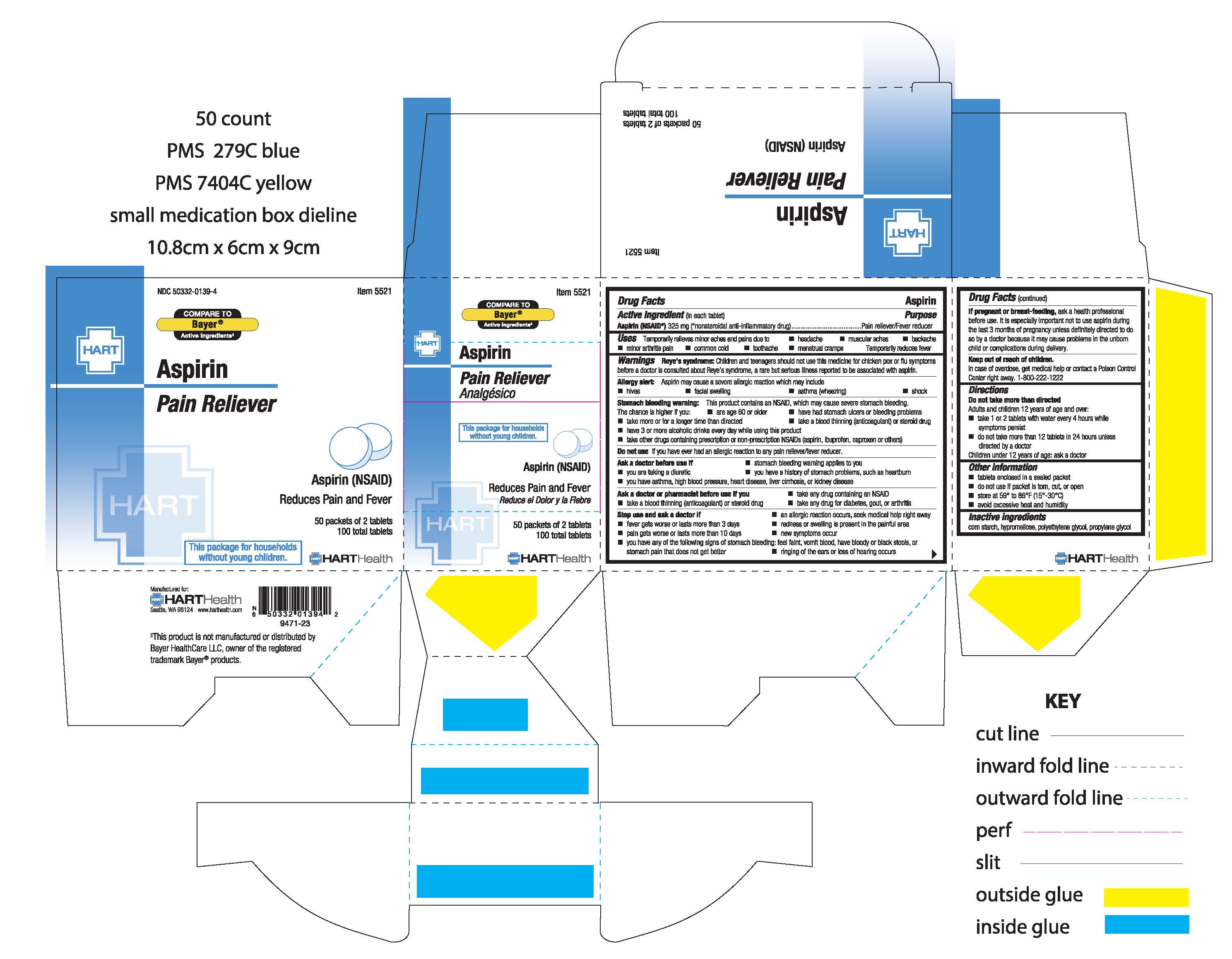 DRUG LABEL: ASPIRIN
NDC: 50332-0139 | Form: TABLET
Manufacturer: HART Health
Category: otc | Type: HUMAN OTC DRUG LABEL
Date: 20260114

ACTIVE INGREDIENTS: ASPIRIN 325 mg/1 1
INACTIVE INGREDIENTS: STARCH, CORN; HYPROMELLOSE, UNSPECIFIED; POLYETHYLENE GLYCOL, UNSPECIFIED; PROPYLENE GLYCOL

ASPIRIN

Active Ingredient

Aspirin (NSAID)* 325mg (*non-steroidal anti-inflammatory drug)

Purpose

Pain Reliever/Fever Reducer

Uses

Temporarily relieves minor aches and pains due to:

- headache
- backache
- muscular aches
- minor arthritis pain
- common cold
- toothache
- menstrual cramps

Temporarily reduces fever

Warnings

Reye's Syndrome: Children and teenagers should not use this medicine for chicken pox or flu symptoms before a doctor is consulted about Reye's syndrome, a rare but serious illness reported to be associated with aspirin

Allergy altert: Aspirin may cause a several allergic reaction which may include:

- hives
- facial swelling
- asthma (wheezing)
- shock

Stomach bleeding warning: This product contains an NSAID, which may cause severe stomach bleeding. The chance is higher if you:

- are age 60 or older
- have had stomach ulers or bleeding problems
- take more or for a longer time than directed
- take a blood thinning (anticoagulant) or steroid drug
- take other drugs containing prescription or non-prescription NSAIDs (aspirin, ibuprofen, naproxen, others)
- have 3 or more alcholic drinks every day while using this product

Do not use if you have ever had an allergic reaction to any other pain reliever/fever reducer

Ask a doctor before use if:

- stomach bleeding warning applies to you
- you have a history of stomach problems, such as heartburn
- you are taking a diuretic
- you have asthma, high blood pressure, heart disease, liver cirrhosis, or kidney disease

Ask a doctor or pharmacist before use if you:

- take any other drug containing an NSAID
- take a blood thinning (anticoagulant) or steroid drug
- take any drug for diabetes, gout, or arthritis

STOP USE

- an allergic reaction occurs, seek medical help right away
- fever gets worse or lasts more than 3 days
- pain gets worse or lasts more than 10 days
- redness or swelling is present in the painful area
- ringing in the ears or loss of hearing occurs
- new symptoms occur
- you have any of the following signs of stomach bleeding: feel faint, vomit blood, have bloody or black stools, or stomach pain that does not get better

PREGNANCY OR BREAST FEEDING

If pregnant or breast-feeding, ask a health professional before use. It is especially important not to use aspirin during the last 3 months of pregnancy unless definitely directed to do so by a doctor because it may cause problems in the unborn child or complications during delivery

Keep out of reach of children. In case of overdose, get medical help or contact a Poison Control Center right away. 1-800-222-1222

Directions:

Do not take more than directed.

Adults and children 12 years of age and over:

- take 1 or 2 tablets with water every 4 hours while symptoms persist
- do not take more than 12 tablets in 24 hours unless directed by a doctor

Children under 12 years of age: ask a doctor

INACTIVE INGREDIENT

Inactive Ingredients: corn starch, hypromellose, polyethylene glycol, propylene glycol